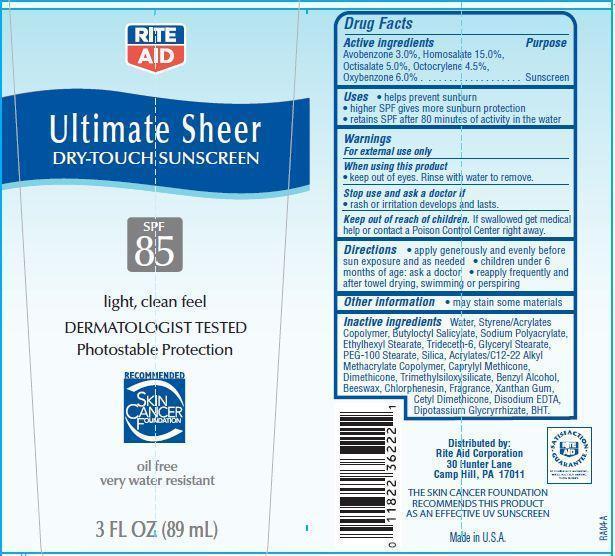 DRUG LABEL: Rite Aid Ultimate Sheer
                
NDC: 11822-9016 | Form: LOTION
Manufacturer: RITE AID CORPORATION
Category: otc | Type: HUMAN OTC DRUG LABEL
Date: 20121206

ACTIVE INGREDIENTS: AVOBENZONE 3 g/100 g; HOMOSALATE 15 g/100 g; OCTISALATE 5 g/100 g; OCTOCRYLENE 4.5 g/100 g; OXYBENZONE 6 g/100 g
INACTIVE INGREDIENTS: WATER; BUTYLOCTYL SALICYLATE; TRIDECETH-6; ETHYLHEXYL STEARATE; GLYCERYL MONOSTEARATE; PEG-100 STEARATE; SILICON DIOXIDE; CAPRYLYL TRISILOXANE; DIMETHICONE; BENZYL ALCOHOL; YELLOW WAX; CHLORPHENESIN; XANTHAN GUM; EDETATE DISODIUM; GLYCYRRHIZINATE DIPOTASSIUM; BUTYLATED HYDROXYTOLUENE

Drug Facts

Active ingredients

Avobenzone 3.0 %

Homosalate 15.0%

Octisalate 5.0%

Octocrylene 4.5%

Oxybenzone 6.0%

Purpose

Sunscreen

Uses

- helps prevent sunburn
- higher SPF gives more sunburn protection
- retains SPF after 80 minutes of activity in the water

Warnings

For external use only

When using this product

- keep out of eyes. Rinse with water to remove.

Stop use and ask a doctor if

- rash or irritation develops and lasts.

Keep out of reach of children

If swallowed, get medical help or contact a Poison Control Center right away.

Directions

- apply generously and evenly before sun exposure and as needed
- children under 6 months of age:ask a doctor
- reapply frequently and after towel drying, swimming or perspiring.

Other Information

- may stain some materials

Inactive Ingredients

Water, Styrene/Acrylates Copolymer, Butyloctyl Salicylate, Glyceryl Stearate, Silica, PEG-100 Stearate, Acrylates/C12-22 Alkyl Methacrylate Copolymer, Caprylyl Methicone, Sodium Polyacrylate, Benzyl Alcohol, Beeswax, Ethylhexyl Stearate, Dimethicone, Cetyl Dimethicone, Xanthan Gum, Trimethylsiloxysilicate, Trideceth-6, Disodium EDTA, Dipotassium Glycyrrhizate, BHT, Chlorphenesin, Fragrance.

Principal Display Panel

RITE AID
Ultimate Sheer
DRY-TOUCH SUNSCREEN
SPF
85
light, clean feel
DERMATOLOGIST TESTED
Photostable Protection
RECOMMENDED
SKIN CANCER FOUNDATION
oil free
very water resistant
3 FL OZ (89 mL)